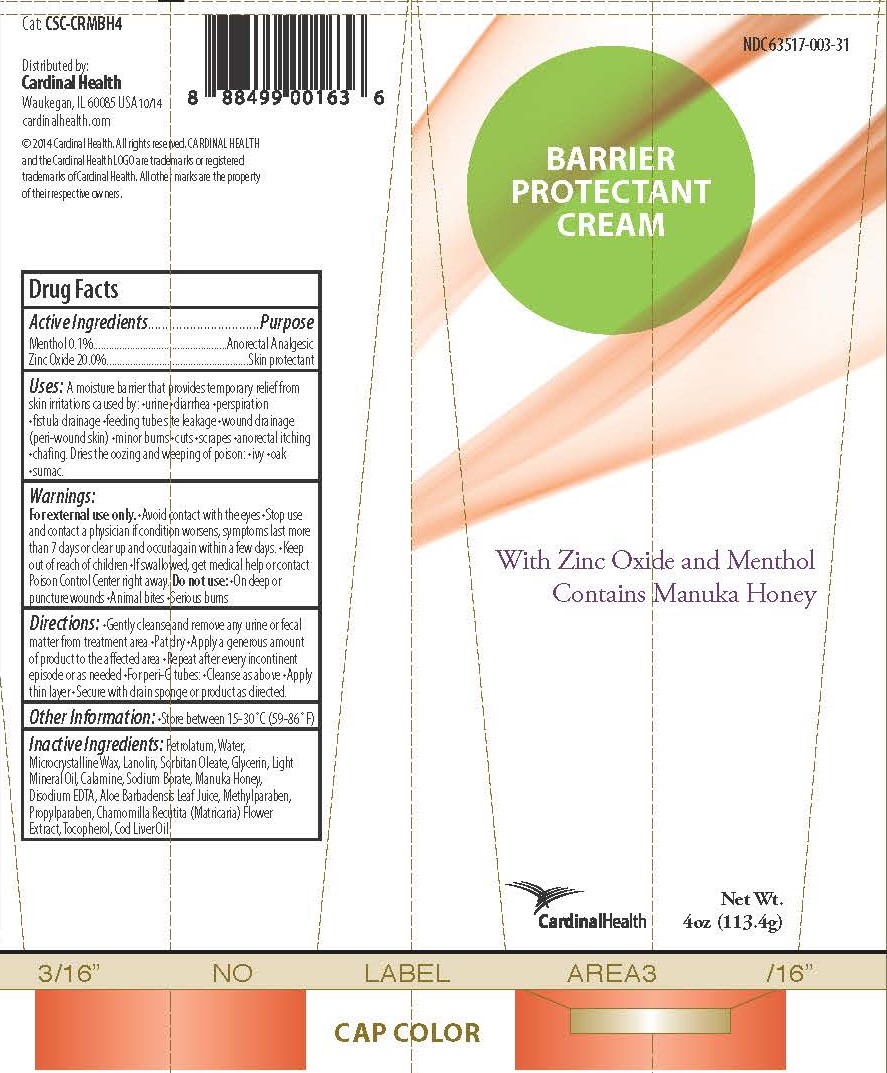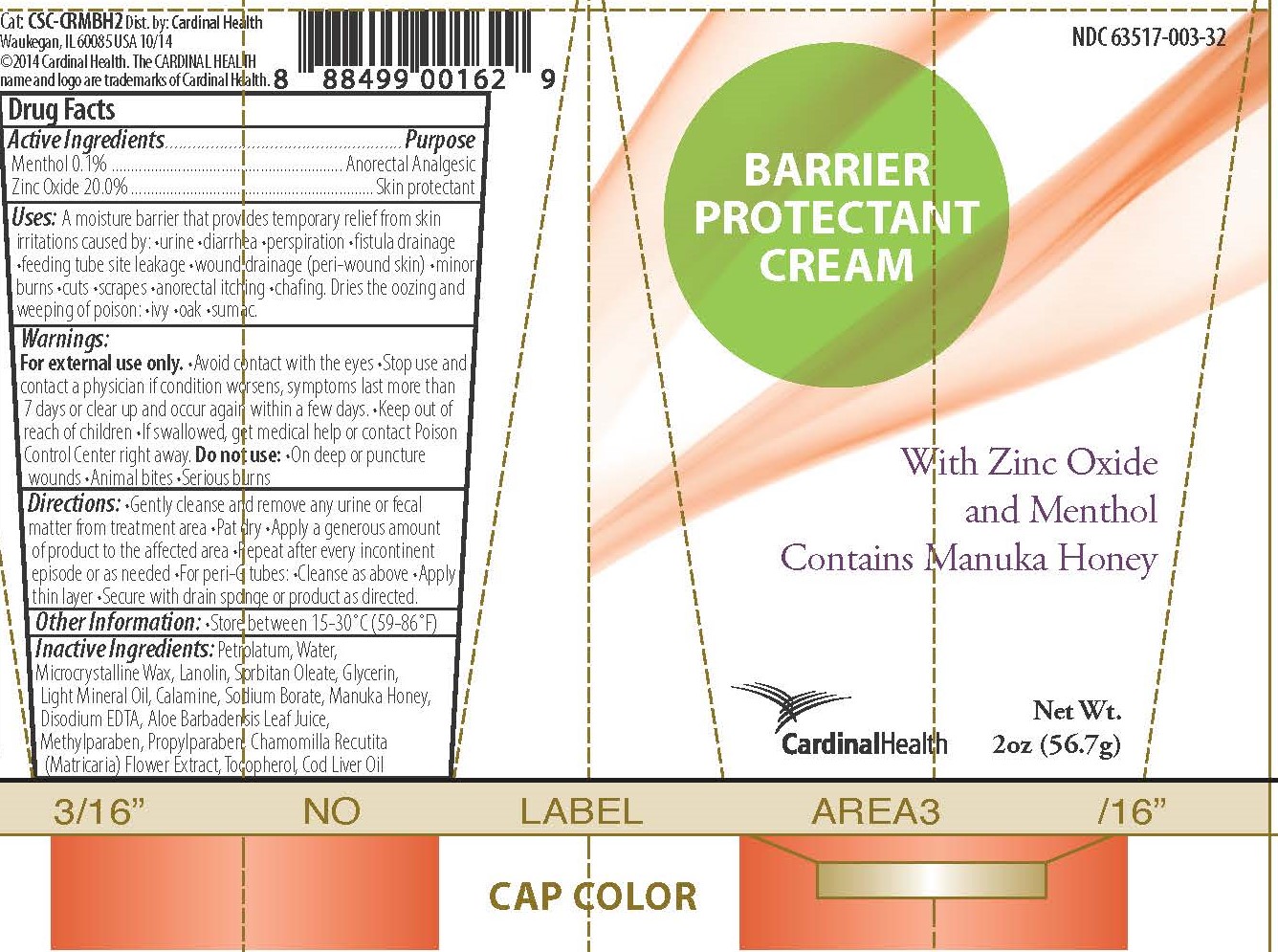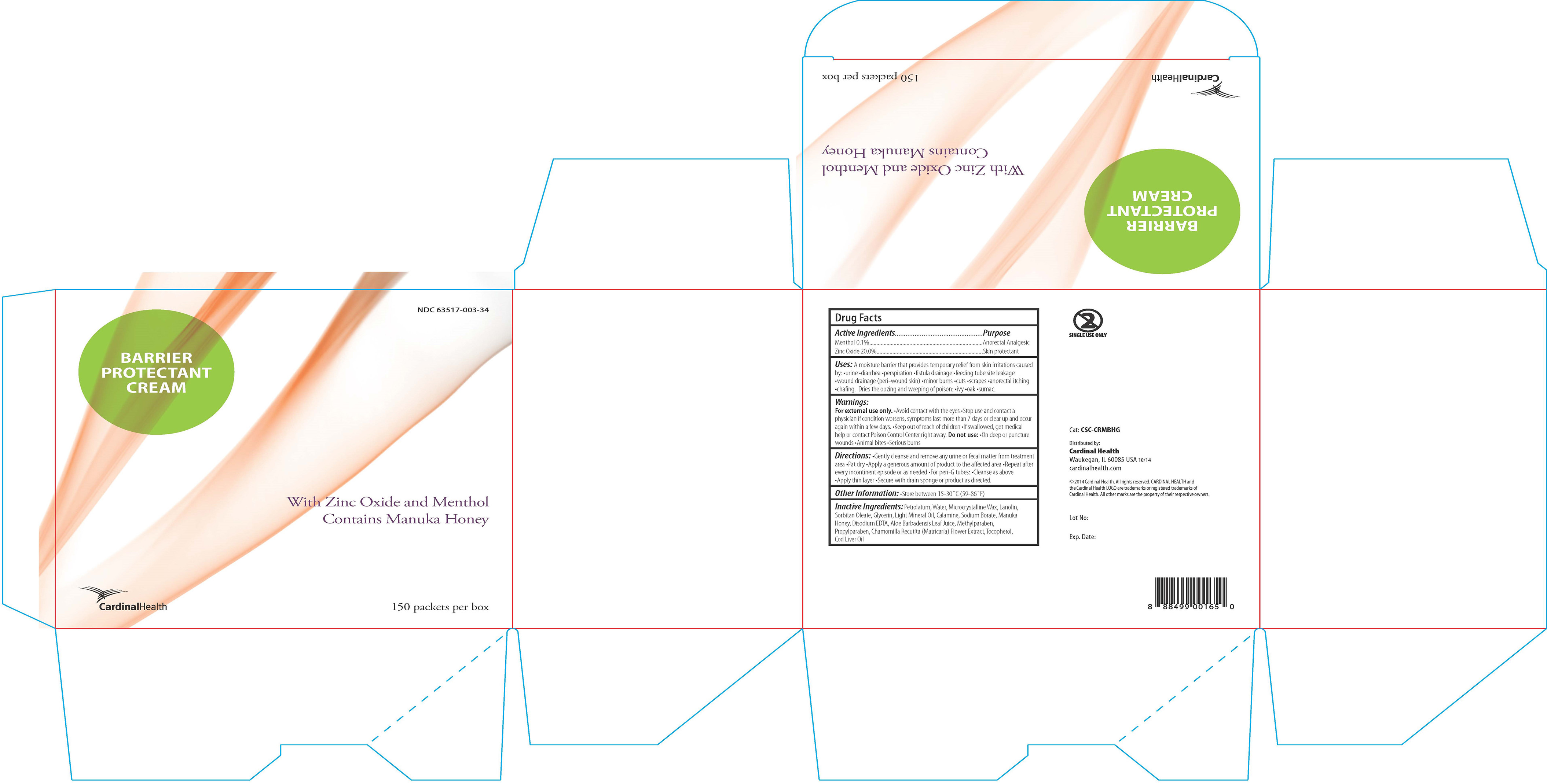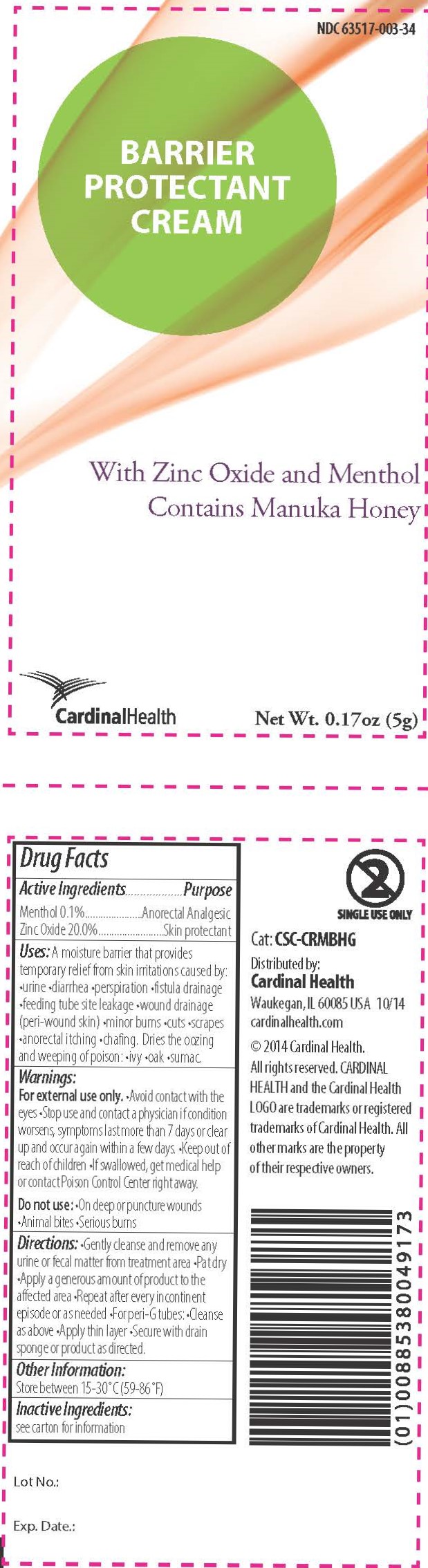 DRUG LABEL: Barrier Protectant Cream
NDC: 63517-003 | Form: OINTMENT
Manufacturer: Cardinal Health
Category: otc | Type: HUMAN OTC DRUG LABEL
Date: 20250821

ACTIVE INGREDIENTS: MENTHOL 1 mg/1 g; ZINC OXIDE 200 mg/1 g
INACTIVE INGREDIENTS: ALOE VERA LEAF; FERRIC OXIDE RED; CHAMOMILE; COD LIVER OIL; EDETATE DISODIUM; GLYCERIN; LANOLIN; LIGHT MINERAL OIL; HONEY; METHYLPARABEN; MICROCRYSTALLINE WAX; PETROLATUM; PROPYLPARABEN; SODIUM BORATE; SORBITAN MONOOLEATE; TOCOPHEROL; WATER

Barrier Protectant Cream

Active ingredients

- Menthol 0.1%
- Zinc oxide 20%

Purpose

- Anorectal analgesic
- Skin protectant

Uses

A moisture barrier that provides temporary relief from skin irritations caused by •urine •diarrhea •perspiration •fistula drainage •feeding tube site leakage •wound drainage (peri-wound skin) •minor burns •cuts •scrapes •anorectal itching •chafing

Dries the oozing and weeping of poison •ivy •oak •sumac

Warnings

For external use only.

- Avoid contact with the eyes
- Stop use and contact a physician if condition worsens, symptoms last more than 7 days, or clear up and occur again within a few days.
- Keep out of reach of children
- If swallowed, get medical help or contact Poison Control Center right away.

Do not use:

- On deep or puncture wounds
- Animal bites
- Serious burns

Keep out of reach of children.

Directions

- Gently cleanse and remove any urine or fecal matter from the treatment area
- Pat dry
- Apply a generous amount of product to the affected area
- Repeat after every incontinent episode or as needed
- For peri-G tubes: •Cleanse as above •Apply thin layer •Secure with drain sponge or product as directed.

Other information

Store between 59°-86°F (15°-30°C)

Inactive Ingredients

Active aloe gel, Calamine, Chamomilla recutita (matricaria) flower extract, Cod liver oil, Disodium EDTA, Glycerin, Lanolin, Light mineral oil, Manuka honey, Methylparaben, Microcrystalline wax, Petrolatum, Propylparaben, Sodium borate, Sorbitan oleate, Tocopherol, Water

Barrier Protectant Cream Labeling

Tube Label (2 oz)

Tube Label (4 oz)

Packet Labels (Box of 150)